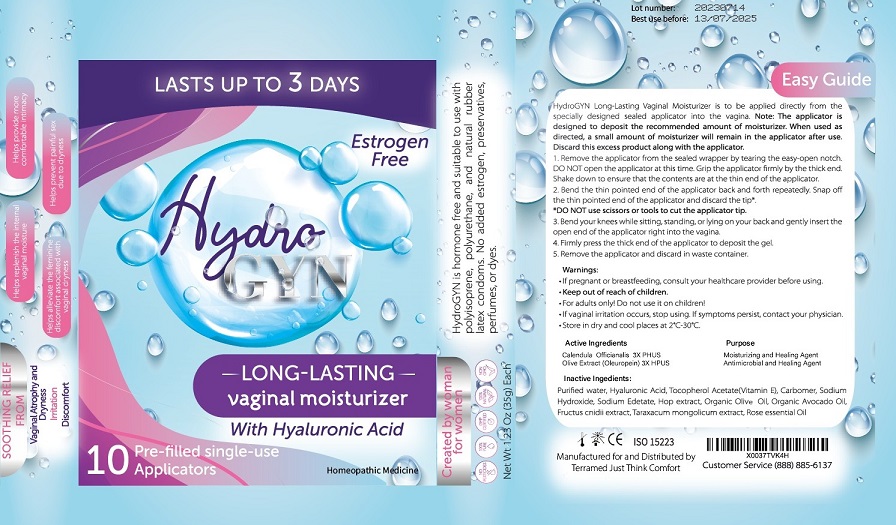 DRUG LABEL: Terramed Just Think Comfort Hydro
NDC: 83004-006 | Form: GEL
Manufacturer: Rida LLC
Category: homeopathic | Type: HUMAN OTC DRUG LABEL
Date: 20250310

ACTIVE INGREDIENTS: OLEUROPEIN 3 [hp_X]/100 mL; CALENDULA OFFICINALIS FLOWERING TOP 3 [hp_X]/100 mL
INACTIVE INGREDIENTS: WATER; HYALURONATE SODIUM; .ALPHA.-TOCOPHEROL ACETATE; POVIDONE-IODINE; CARBOMER HOMOPOLYMER, UNSPECIFIED TYPE; SODIUM HYDROXIDE; EDETATE SODIUM; HOPS; OLIVE OIL; AVOCADO OIL; CNIDIUM MONNIERI FRUIT; TARAXACUM MONGOLICUM WHOLE

Drug Facts

Active Ingredient Purpose

Olive Extract (oleuropein) 3X HPUS Moisturing and Healing Agent

Calendula Officinalis 3X HPUS Anti-microbial and Healing agent

Uses

This product is intended to relieve symptoms associated with known bacterial vaginosis infecions, including fishy odor, excess discharge, irritation and burning while urinating.

Warnings

- For vaginal use only.
- If pregnant or breast-feeding ask a healthcare professional before use.
- Keep out of the reach of childrenIf swallowed, get medical help or contact Poison Control Center right away.
- For adults only. Do not use it on children.
- If vaginal irritation occurs, stop using. If symptoms persist, contact your physician.
- Store in dry and cool place at 2°-30°C

Directions

For individuals aged 12 and older:

- Remove the applicator from the sealed wrapper by tearing the easy-open notch. DO NOT open the applicator at this time. Grip the applicator firmly by the thick end. Shake down to ensure that the contents are at the thin end of the applicator.
- Bend the thin pointed end of the applicator back and forth repeatedly. Snap off the thin pointed end of the applicator and discard the tip.
- DO NOT use scissors or tools to cut the applicator tip
- Bend your knees while sitting, standing or lying on your back and gently insert the open end of the applicator right into the vagina.
- Firmly press the thick end of the applicator to deposit the gel.
- Remove the applicator and discard in waste container.

Inactive Ingredients

Purified water, povidone-iodine, Hyaluronic Acid, Tocopherol Acetate (vitamin E), Carbomer, Sodium Hydroxideb, Sodium Edetate, Hop Extract, Organic olive oil, Organic Avocado oil, Fructus Cnidii Extract, Taraxacum Mongolicum Extract

Other information

Please note that this treatment consists of 7 doses. While many women may not experience complete symptom relief within just two days, most will notice some improvement in that timeframe and should expect complete relief within seven days.